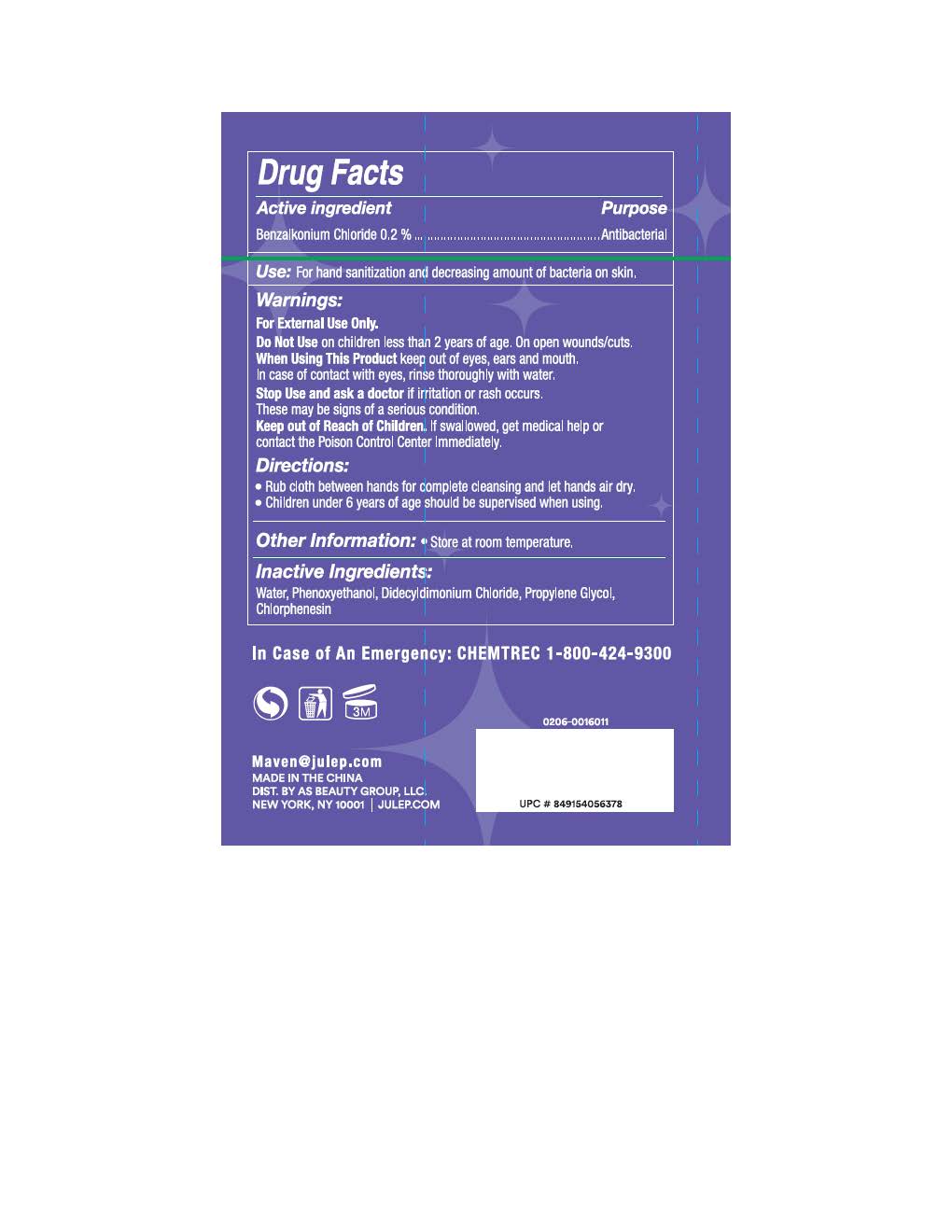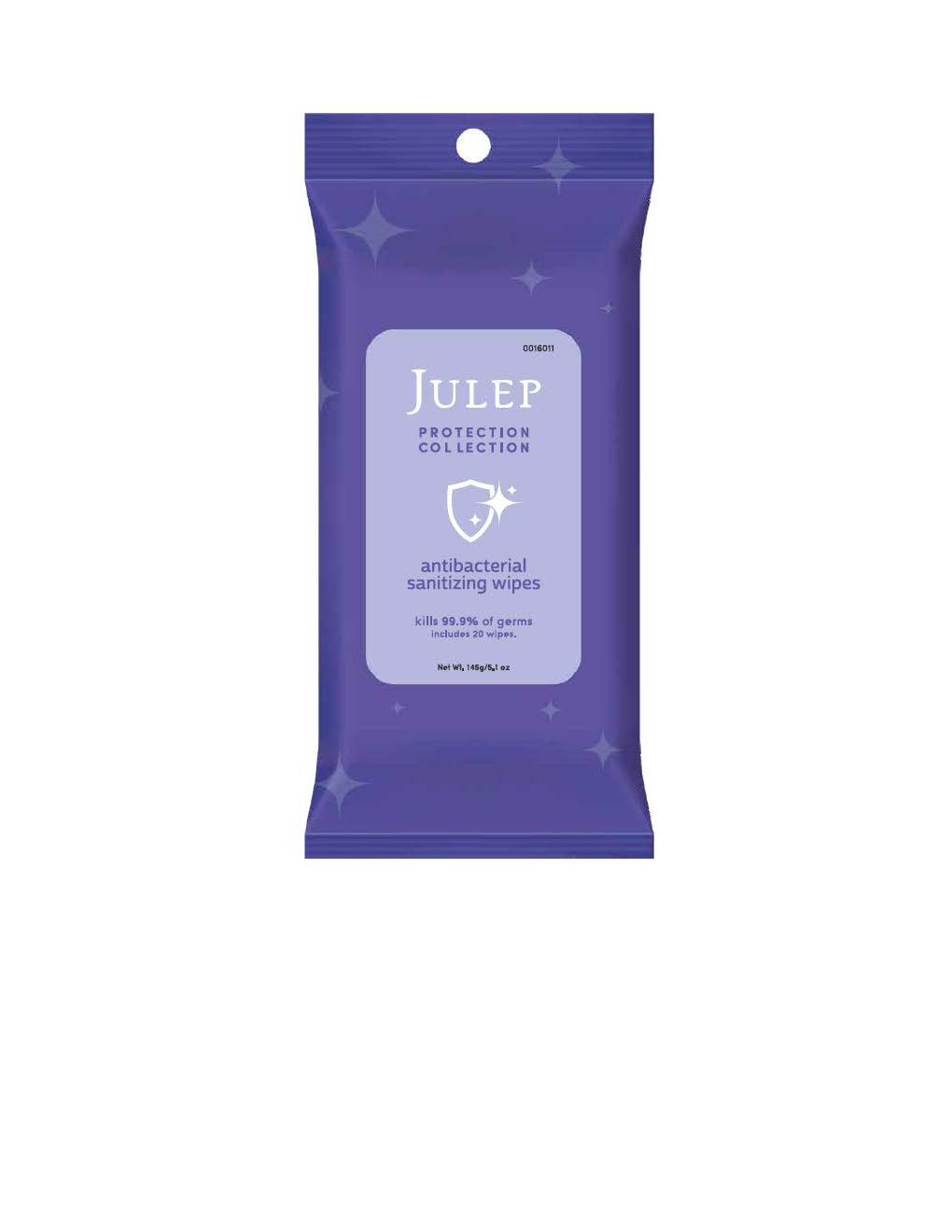 DRUG LABEL: Antibacterial Hand Wipes
NDC: 74884-120 | Form: CLOTH
Manufacturer: AS Beauty
Category: otc | Type: HUMAN OTC DRUG LABEL
Date: 20200518

ACTIVE INGREDIENTS: BENZALKONIUM CHLORIDE 0.2 g/0.2 g
INACTIVE INGREDIENTS: PROPYLENE GLYCOL; CHLORPHENESIN; PHENOXYETHANOL; WATER; DIDECYLDIMONIUM CHLORIDE

Antibacterial Wipe

Usage

Rub hands together for cmplete cleansing and let air dry.

Non actives

Water, Phenoxyethanol, Didecyldimonium Chloride, Propylen Glycol, Chlorphenesin

Indications with Usage

Stop usage if a rash or irritation occurs.

On Children

Keep out of reach of Children

Function

Antibacterial

Warnings

For External Use Only. Keep out of Eyes, Ears, Mouths. Do not use on open wounds or cuts.